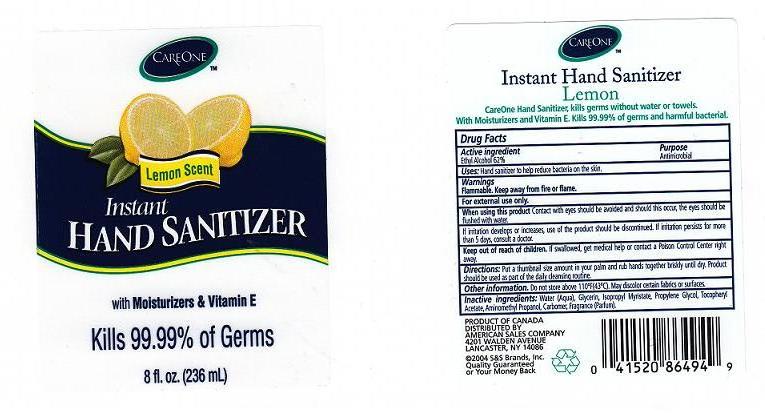 DRUG LABEL: CAREONE INSTANT HAND SANITIZER LEMON
NDC: 41520-227 | Form: GEL
Manufacturer: AMERICAN SALES COMPANY
Category: otc | Type: HUMAN OTC DRUG LABEL
Date: 20110114

ACTIVE INGREDIENTS: ALCOHOL 62 mL/100 mL
INACTIVE INGREDIENTS: WATER; GLYCERIN; ISOPROPYL MYRISTATE; PROPYLENE GLYCOL; .ALPHA.-TOCOPHEROL ACETATE, D-; AMINOMETHYLPROPANOL; CARBOMER 934

DRUG FACTS

ACTIVE INGREDIENT

ETHYL ALCOHOL 62 PERCENT

PURPOSE

ANTIMICROBIAL

USES

HAND SANITIZER TO HELP REDUCE BACTERIA ON THE SKIN.

WARNINGS

FLAMMABLE. KEEP AWAY FROM FIRE OR FLAME.
FOR EXTERNAL USE ONLY.

WHEN USING THIS PRODUCT

CONTACT WITH EYES SHOULD BE AVOIDED AND SHOULD THIS OCCUR, THE EYES SHOULD BE FLUSHED WITH WATER.

STOP USE

IF IRRITATION DEVELOPS OR INCREASES, USE OF THE PRODUCT SHOULD BE DISCONTINUED. IF IRRITATION PERSISTS FOR MORE THAN 5 DAYS, CONSULT A DOCTOR.

KEEP OUT OF REACH OF CHILDREN

IF SWALLOWED, GET MEDICAL HELP OR CONTACT A POISON CONTROL CENTER IMMEDIATELY.

DIRECTIONS

PUT A THUMBNAIL SIZE AMOUNT IN YOUR PALM AND RUB HANDS TOGETHER BRISKLY UNTIL DRY. PRODUCT SHOULD BE USED AS PART OF THE DAILY CLEANSING ROUTINE.

OTHER INFORMATION

DO NOT STORE ABOVE 110 DEGREES FAHRENHEIT OR 43 DEGREES CELSIUS. MAY DISCOLOR CERTAIN FABRICS OR SURFACES.

INACTIVE INGREDIENT

WATER, GLYCERIN, ISOPROPYL MYRISTATE, PROPYLENE GLYCOL, TOCOPHERYL ACETATE, AMINOMETHYL PROPANOL, CARBOMER, FRAGRANCE.